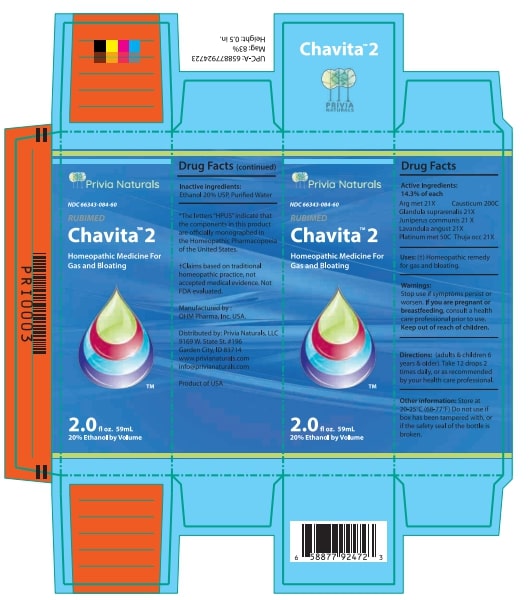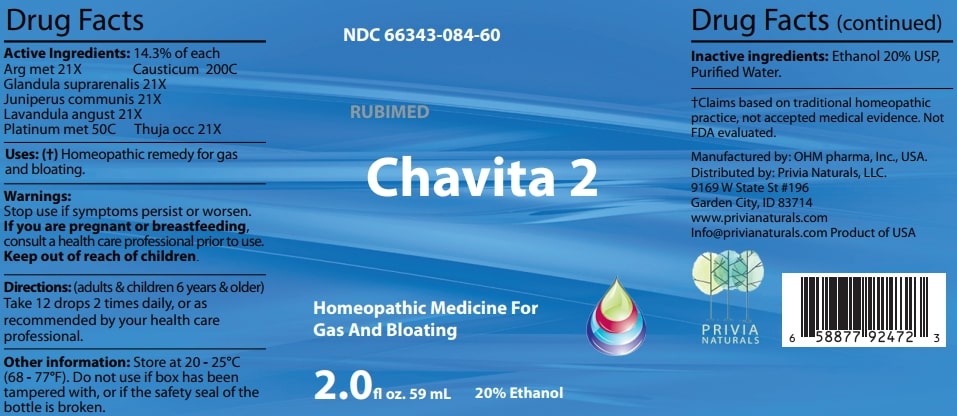 DRUG LABEL: Chavita 2
NDC: 66343-084 | Form: LIQUID
Manufacturer: RUBIMED AG
Category: homeopathic | Type: HUMAN OTC DRUG LABEL
Date: 20241029

ACTIVE INGREDIENTS: SILVER 21 [hp_X]/60 mL; CAUSTICUM 200 [hp_C]/60 mL; SUS SCROFA ADRENAL GLAND 21 [hp_X]/60 mL; JUNIPER BERRY 21 [hp_X]/60 mL; LAVANDULA ANGUSTIFOLIA WHOLE 21 [hp_X]/60 mL; PLATINUM 50 [hp_C]/60 mL; THUJA OCCIDENTALIS LEAFY TWIG 21 [hp_X]/60 mL
INACTIVE INGREDIENTS: ALCOHOL; WATER

Chavita 2

ACTIVE INGREDIENT

Drug Facts Active Ingredients: (HPUS*) 16.7% of each

Arg met 21X Causticum 200C

Glandula suprarenalis 21X

Juniperus communis 21X

Lavandula angust 21X

Platinum met 50C Thuja occ 21X

*The letters "HPUS" indicate that the components in this product are officially monographed in the Homeopathic Pharmacopoeia of the United States. †Claims based on traditional homeopathic practice, not accepted medical evidence. Not FDA evaluated.

INDICATIONS AND USAGE

Uses: (†) Homeopathic remedy for gas and bloating.

Warnings:

Stop use if symptoms persist or worsen.

If you are pregnant or breastfeeding,consult a healthcare professional prior to use.

Keep out of reach of children.

DOSAGE AND ADMINISTRATION

Directions: (adults & children 6 years & older)

Take 12 drops 2 times daily, or as recommended by your health care professional.

Other information: Store at 20 - 25°C

(68 - 77°F.) Do not use if box has been

tampered with, or if the safety seal of the

bottle is broken.

Inactive ingredients:Ethanol 20% USP,

Purified Water.

QUESTIONS

Manufactured by: OHM pharma, Inc, USA.

Distributed by: Privia Naturals, LLC.

9169 W State St #196

Garden City, ID 83714

www.privianaturals.com

Info@privianaturals.com Product of USA.

PACKAGE LABEL

NDC 66343-084-60

RUBIMED

Chavita 2

Homeopathic Medicine For

Gas And Bloating

2.0 fl oz. 59mL 20% Ethanol

PURPOSE

Homeopathic Medicine For

Gas And Bloating